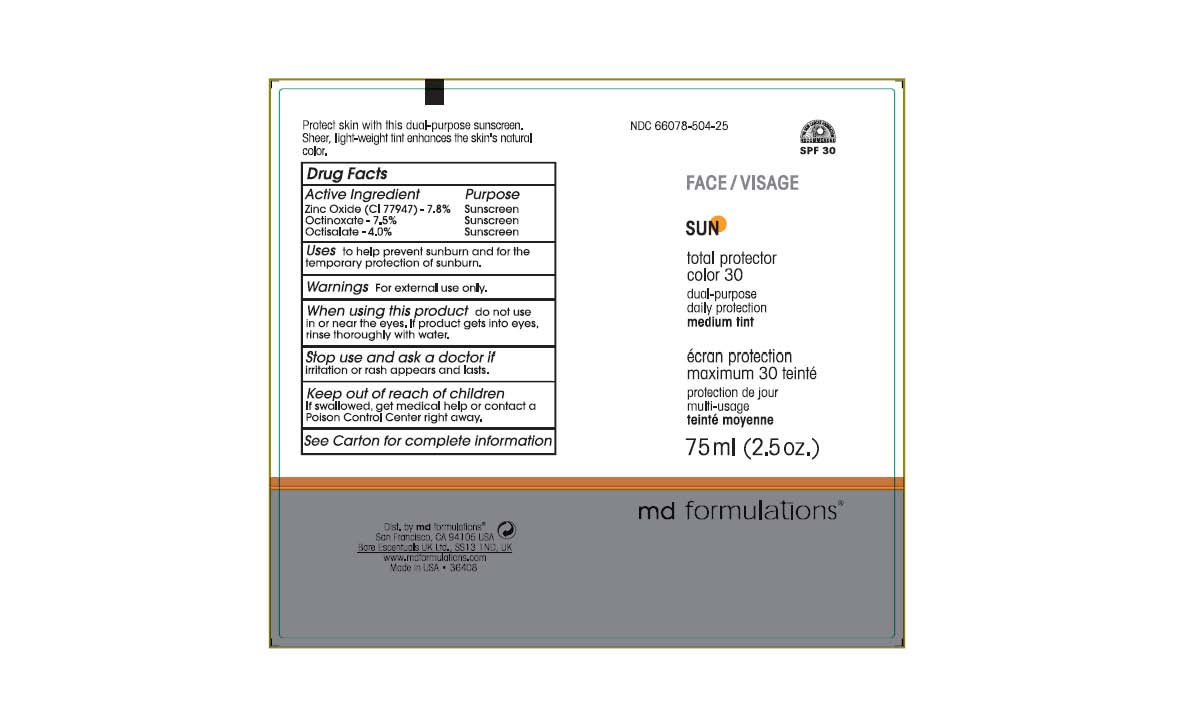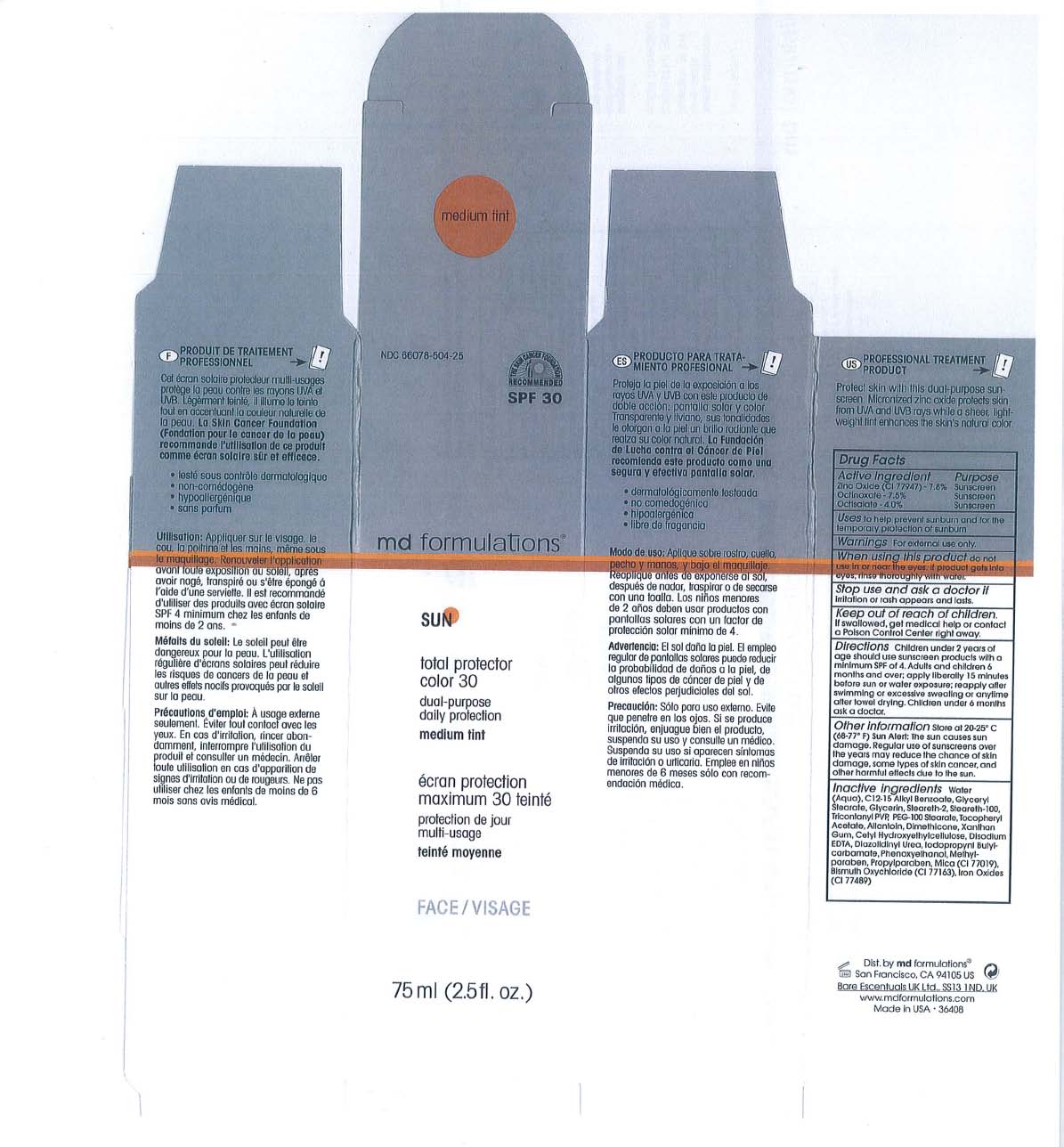 DRUG LABEL: Total Protector Color 30 Medium Tint
NDC: 66078-504 | Form: CREAM
Manufacturer: MD Formulation
Category: otc | Type: HUMAN OTC DRUG LABEL
Date: 20110525

ACTIVE INGREDIENTS: Octinoxate 7.5 g/100 g; Zinc Oxide 7.8 g/100 g; Octisalate 4.0 g/100 g
INACTIVE INGREDIENTS: Glycerin; Allantoin; EDETATE DISODIUM; Xanthan Gum; CETYL HYDROXYETHYLCELLULOSE (350000 MW); Methylparaben; GLYCERYL MONOSTEARATE; Steareth-2; PEG-100 Stearate; TRIACONTANYL PVP (WP-660); ALKYL (C12-15) BENZOATE; .ALPHA.-TOCOPHEROL ACETATE, DL-; Propylparaben; TRIETHOXYCAPRYLYLSILANE; Mica; BISMUTH OXYCHLORIDE; BROWN IRON OXIDE; DIAZOLIDINYL UREA; Iodopropynyl Butylcarbamate; Phenoxyethanol; FERRIC OXIDE YELLOW; FERROSOFERRIC OXIDE

SUN Total Protector Color 30 Medium Tint

Active Ingredient Purpose

Zinc Oxide - 7.8% Sunscreen
Octinoxote - 7.5% Sunscreen
Octisalate - 4.0% Sunscreen

When using this product do not use in or near the eyes. If product gets into eyes, rinse thoroughly with water.

Warnings For external use only.

Stop use and ask a doctor if Irritation of rash appears and lasts.

KEEP OUT OF REACH OF CHILDREN

If swallowed, get medical help or contact a Polson Control Center right away .

INACTIVE INGREDIENT

Inactive ingredients Purified Waler (Aqua), C 12-15 Alkyl Benzoate, Glyceryl Stearate, Glycerin,Steareth-2, Steareth-100, TricontanylPVP, PEG-100 Stearate, Tocopheryl Acetate, Allantoin, Dimethicone, Xanthan Gum, Cetyl Hydroxyethylcellulose, Disodium EDTA, Diazolidinyl Urea, Iodopropynl Butylcarbamate, Phenoxyethanol, Methylparaben, Propylparaben, Mica(CI 77019), Bismuth Oxychloride (CI 77163), Iron Oxides (CI 77489)

Active Ingredient Purpose
Zinc Oxide - 7.8% Sunscreen
Octinoxote - 7.5% Sunscreen
Octisalate - 4.0% Sunscreen

DOSAGE AND ADMINISTRATION

Directions Children under 2 years of age should use sunscreen products with a minimum SPF of 4. Adults and children 6 months and over; apply liberally 15 minutes before sun or water exposure; reapply after swimming or excessive sweating or anytime after towel drying. Children under 6 months ask a doctor.